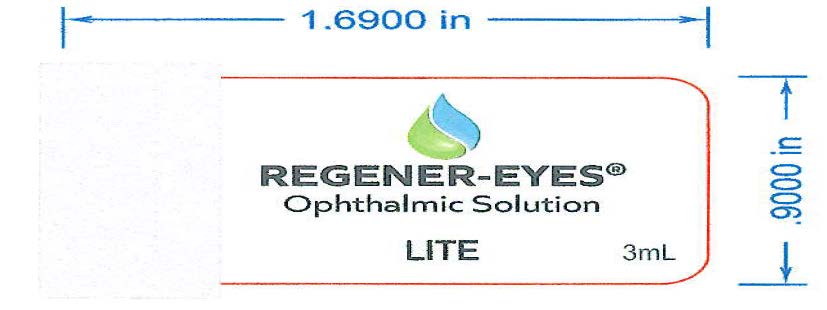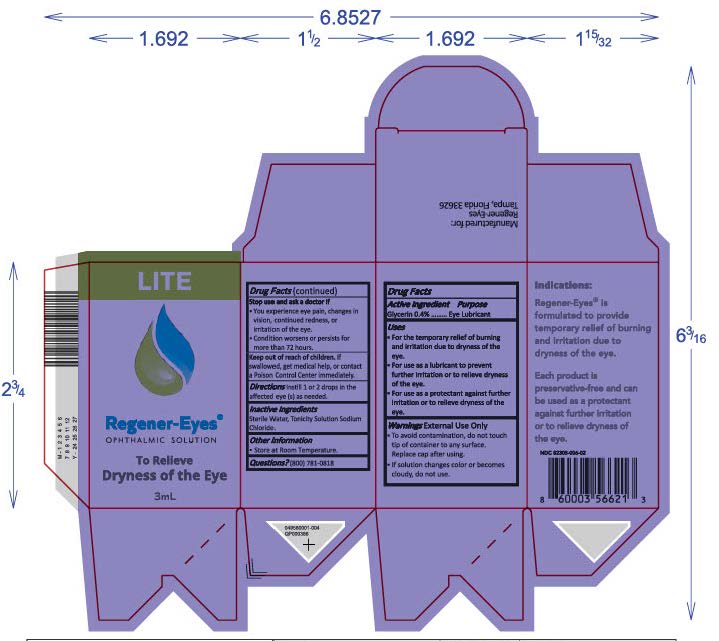 DRUG LABEL: Regener-Eyes
NDC: 82305-006 | Form: SOLUTION/ DROPS
Manufacturer: Regenerative Processing Plant, LLC
Category: otc | Type: HUMAN OTC DRUG LABEL
Date: 20250320

ACTIVE INGREDIENTS: GLYCERIN 12 mg/3 mL
INACTIVE INGREDIENTS: WATER; SODIUM CHLORIDE

Active ingredient

Glycerin 0.4%

PURPOSE

Eye Lubricant

Uses

- For the temporary relief of burning and irritation due to dryness of the eye.
- For use as a lubricant to prevent further irritation or to relieve dryness of the eye.
- For use as a protectant against further irritation or to relieve dryness of the eye.

Warnings

Warnings External Use Only

- To avoid contamination, do not touch tip of the bottle closure to any surface(s) including the eye or the skin.
- Do not use if solution changes color or becomes cloudy.

Stop use and ask a doctor If

- You experience eye pain, changes in vision, continued redness, or irritation of the eye.
- Condition worsens or persists for more than 72 hours.

Keep out of reach of children. If swallowed, get medical help, or contact a Poison Control Center immediately.

Directions

Directions Instill 1 to 2 drops, one to four times per day in each eye, or as recommended by your eye care professional.

RECENT MAJOR CHANGES

Instill 1 or 2 drops in the affected eye(s) as needed.

Inactive ingredients

Sterile Water, Tonicity Solution Sodium Chloride.

Other information

- Store at Room Temperature.

Questions?

Questions? (800) 781-0818